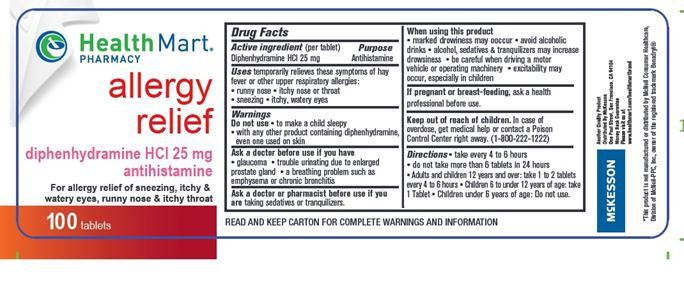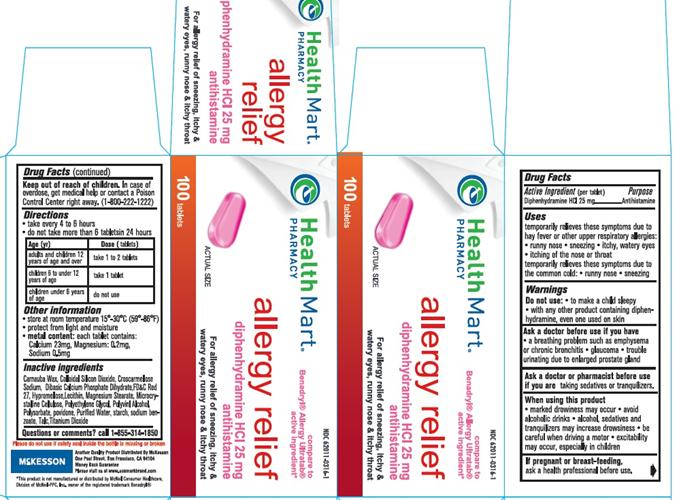 DRUG LABEL: Allergy
NDC: 62011-0316 | Form: TABLET
Manufacturer: Mckesson
Category: otc | Type: HUMAN OTC DRUG LABEL
Date: 20161213

ACTIVE INGREDIENTS: DIPHENHYDRAMINE HYDROCHLORIDE 25 mg/1 1
INACTIVE INGREDIENTS: CARNAUBA WAX; SILICON DIOXIDE; CROSCARMELLOSE SODIUM; D&C RED NO. 27; DIBASIC CALCIUM PHOSPHATE DIHYDRATE; HYPROMELLOSES; MAGNESIUM STEARATE; CELLULOSE, MICROCRYSTALLINE; POLYETHYLENE GLYCOLS; POLYSORBATE 80; TITANIUM DIOXIDE; POLYVINYL ALCOHOL; POVIDONE; STARCH, CORN; SODIUM BENZOATE; TALC

DIPHENHYDRAMINE HCl 25mg, USP

Active Ingredient

(in each tablet)

Diphenhydramine HCl 25 mg

Purpose

Antihistamine

Uses

temporarily relieves these symptoms of hay fever or other upper respiratory allergies:

- runny nose
- itching of the nose or throat
- sneezing
- itchy, watery eyes
  temporarily relieves these symptoms due to the common cold:
- runny nose
- sneezing

Warnings

Do not use

- to make a child sleepy
- with any other product containing diphenhydramine, even one used on skin
  Ask a doctor before use if you have
- a breathing problem such as emphysema or chronic bronchitis
- glaucoma
- trouble urinating due to an enlarged prostate gland
  Ask a doctor or pharmacist before use if you are taking sedatives or tranquilizers
  When using this product
- you may get very drowsy
- avoid alcoholic drinks
- alcohol, sedatives & tranquilizers may increase drowsiness
- be careful when driving a motor vehicle or operating machinery
- excitability may occur, especially in children
  If pregnant or breast-feeding, ask a health professional before use.

Keep out of reach of children.

In case of overdose, get medical help or contact a Poison Control Center right away. (1-800-222-1222)

Directions

- take every 4 to 6 hours
- do not take more than 6 tablets in 24 hours
  Age (Yr) | Dose (tablets)
  Adults and children 12 years of age and over | Take 1 to 2 tablets
  Children 6 to under 12 years of age | Take 1 tablet
  Children under 6 years of age | do not use

Other Information

- store at 25°C(77 °F) excusrsions permitted between 15°-30°C (59°-86°F)
- protect from light and moisture
- metal content: each tablet contains: Calcium 23mg, Magnesium: 0.2 mg, sodium 0.5 mg

Inactive Ingredients

Carnauba Wax, Colloidal silion dioxide, croscarmellose sodium, D&C red #27 al lake, dibasic calcium phosphate dihydrate, hypromellose, Lecithin, magnesium stearate, microcrystalline cellulose, polyethylene glycol, Polyvinyl Alcohol, polysorbate, Povidone, Purified water, starch, sodium benozoate, talc,Titanium Dioxide

Questions or Comments

Call 1-855-314-1850

READ AND KEEP CARTON FOR COMPLETE WARNING AND INFORMATION

PACKAGE LABEL.PRINCIPAL DISPLAY PANEL

NDC 62011-0316-1